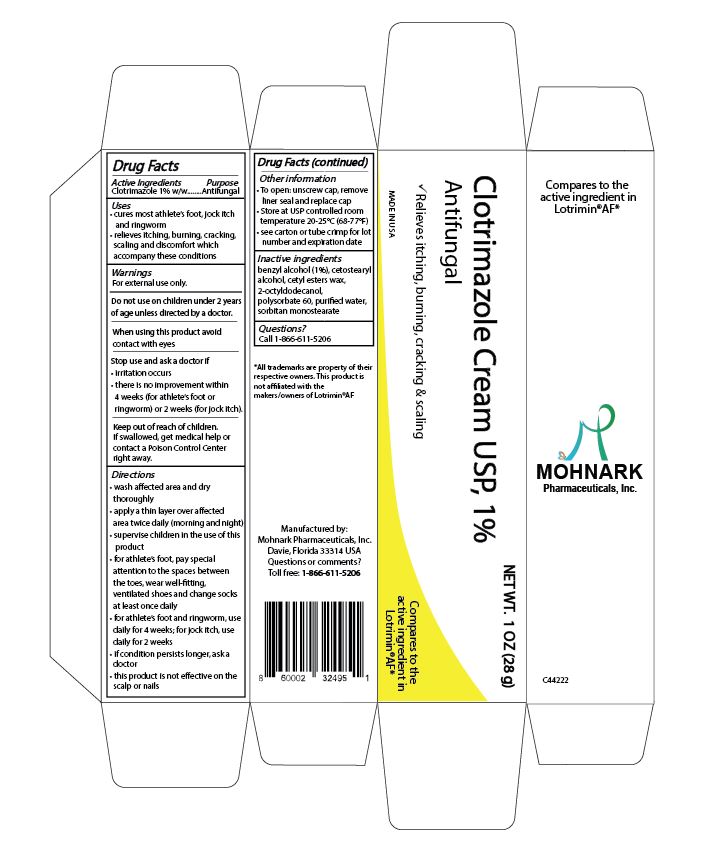 DRUG LABEL: Clotrimazole 1% Topical Antifungal Cream
NDC: 73715-004 | Form: CREAM
Manufacturer: Mohnark Pharmaceuticals Inc.
Category: otc | Type: HUMAN OTC DRUG LABEL
Date: 20250720

ACTIVE INGREDIENTS: CLOTRIMAZOLE 1 g/100 g
INACTIVE INGREDIENTS: BENZYL ALCOHOL 1 g/100 g; WATER 69.5 g/100 g; POLYSORBATE 60 1.5 g/100 g

Clotrimazole 1% Topical Antifungal Cream

ACTIVE INGREDIENT

Clotrimazole 1%

PURPOSE

Antifungal

cures most athlete's foot, jock itch and ringworm

relieves itching, burning, cracking, scaling and discomfort which accompany these conditions.

WARNINGS

For external use only

Do not use on children under 2 years of age unless directed by a doctor

When using this product avoid contact with eyes

Stop use and ask a doctor if

- irritation occurs
- there is no improvement within 4 weeks (for athlete's foot or ringworm) or 2 weeks (for jock itch)

Keep out of reach of children.

If swallowed, get medical help or contact a Poison Control Center right away.

STOP USE AND ASK DOCTOR IF

irritation occurs
there is no improvement within 4 weeks (for athlete's foot or ringworm) or 2 weeks (for jock itch)

DIRECTIONS

- wash affected area and dry thoroughly
- apply a thin layer over affected area twice daily (morning and night)
- supervise children in the use of this product
- for athlete's foot, pay special attention to the spaces between the toes, wear well fitting, ventilated shoes and change socks at least once daily
- for athlete's foot and ringworm, use daily for 4 weeks; for jock itch, use daily for 2 weeks
- if condition persists longer, ask a doctor
- this product is not effective on the scalp or nails

OTHER INFORMATION

- To open: unscrew cap, remove liner seal and replace cap
- Store at USP controlled room temperature 20-25°C (68-77°F)
- see carton or tube crimp for lot number and expiration date

INACTIVE INGREDIENTS

benzyl alcohol (1%), cetostearyl alcohol, cetyl esters wax, 2-octyldodecanol, polysorbate 60, purified water, sorbitan monostearate

DOSAGE AND ADMINISTRATION

10 milligrams/gram per application

DOSAGE AND ADMINISTRATION

added dosage information

INDICATIONS AND USAGE

Adults and children 2 years and older: apply externally to the affected area twice a day (morning and night).
Children under 2 years of age: consult a doctor

KEEP OUT OF REACH OF CHILDREN

If swallowed, get medical help or contact a Poison Control Center right away